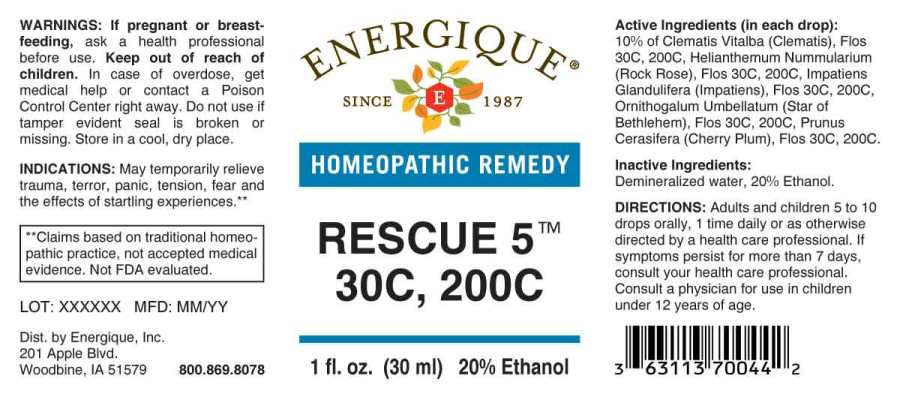 DRUG LABEL: Rescue 5
NDC: 44911-0295 | Form: LIQUID
Manufacturer: Energique, Inc.
Category: homeopathic | Type: HUMAN OTC DRUG LABEL
Date: 20230616

ACTIVE INGREDIENTS: CLEMATIS VITALBA FLOWER 30 [hp_C]/1 mL; HELIANTHEMUM NUMMULARIUM FLOWER 30 [hp_C]/1 mL; IMPATIENS GLANDULIFERA FLOWER 30 [hp_C]/1 mL; ORNITHOGALUM UMBELLATUM FLOWERING TOP 30 [hp_C]/1 mL; PRUNUS CERASIFERA FLOWER 30 [hp_C]/1 mL
INACTIVE INGREDIENTS: WATER; ALCOHOL

Drug Facts:

ACTIVE INGREDIENTS:

(in each drop): 10% of Clematis Vitalba (Clematis), Flos 30C, 200C, Helianthemum Nummularium (Rock Rose), Flos 30C, 200C, Impatiens Glandulifera (Impatiens), Flos 30C, 200C, Ornithogalum Umbellatum (Star of Bethlehem), Flos 30C, 200C, Prunus Cerasifera (Cherry Plum), Flos 30C, 200C.

INDICATIONS:

May temporarily relieve trauma, terror, panic, tension, fear and the effects of startling experiences.**

**Claims based on traditional homeopathic practice, not accepted medical evidence. Not FDA evaluated.

WARNINGS:

If pregnant or breast-feeding, ask a health professional before use.
Keep out of reach of children. In case of overdose, get medical help or contact a Poison Control Center right away.
Do not use if tamper evident seal is broken or missing. Store in a cool, dry place.

Keep out of reach of children. In case of overdose, get medical help or contact a Poison Control Center right away.

DIRECTIONS:

Adults and children 5 to 10 drops orally, 1 time daily or as otherwise directed by a health care professional. If symptoms persist for more than 7 days, consult your health care professional. Consult a physician for use in children under 12 years of age.

INDICATIONS:

May temporarily relieve trauma, terror, panic, tension, fear and the effects of startling experiences.**

**Claims based on traditional homeopathic practice, not accepted medical evidence. Not FDA evaluated.

INACTIVE INGREDIENTS:

Demineralized water, 20% Ethanol.

QUESTIONS:

Dist. by Energique, Inc.
201 Apple Blvd
Woodbine, IA 51579 800-869-8078

PACKAGE LABEL DISPLAY:

ENERGIQUE

SINCE 1987

HOMEOPATHIC REMEDY

RESCUE 5

30C, 200C

1 fl. oz. (30 ml)